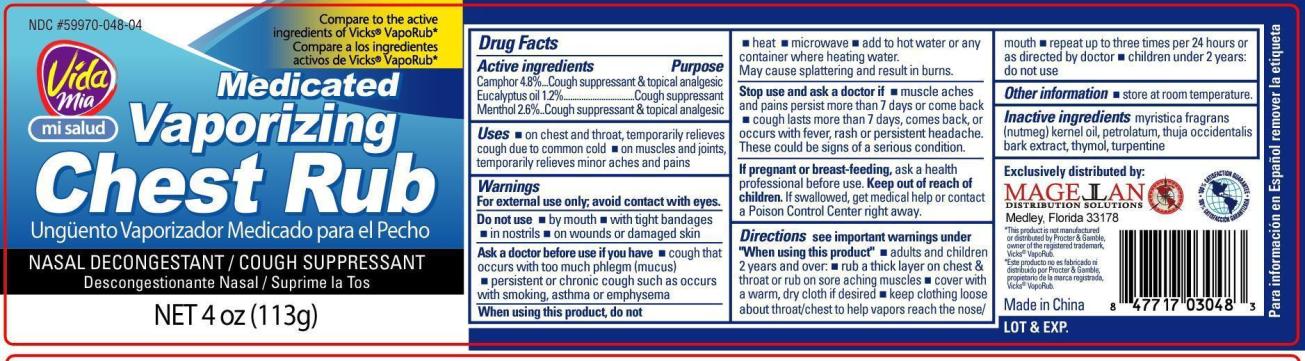 DRUG LABEL: Vaporizing Chest Rub
NDC: 59970-048 | Form: GEL
Manufacturer: Narvarro Discount Pharmarcies,LLC
Category: otc | Type: HUMAN OTC DRUG LABEL
Date: 20120815

ACTIVE INGREDIENTS: CAMPHOR (SYNTHETIC) 4.8 g/100 g; EUCALYPTUS OIL 2.6 g/100 g; MENTHOL 1.2 g/100 g
INACTIVE INGREDIENTS: NUTMEG OIL; PETROLATUM; THUJA OCCIDENTALIS BARK; THYMOL; TURPENTINE

Drug Facts

Active ingredients

Camphor 4.8%

Eucalyptus Oil 1.2%

Menthol 2.6%

Purpose

Cough suppressant and topical analgesic

Cough suppressant

Cough suppressant and topical analgesic

Uses

- On chest and throat, temporarily relieves cough due to common cold
- On muscles and joints, temporarily relieves minor aches and pains

Warnings

For external use only; avoid contact with eyes.

Do not use

- by mouth
- with tight bandages
- in nostrils
- on wounds or damaged skin

Ask a doctor before use if you have

- cough that occurs with too much phlegm (mucus)
- persistent or chronic cough such as occurs with smoking, asthma or emphysema

When using this product, do not

- heat
- microwave
- add to hot water or any container where heating water.

May cause splattering and result in burns.

Stop use and ask a doctor if

- muscle aches and pains persist more than 7 days or come back
- cough lasts for more than 7 days, comes back or occurs with fever, rash or persistent headache.
  These could be signs of a serious condition.

If pregnant or breast-feeding,

ask a health professional before use.

Keep out of reach of children.

If swallowed, get medical help or contact a Poison Control Center right away.

Directions

see important warnings under "When using this product"

- adults and children 2 years and over:
- Apply a thick layer on chest and throat or rub on sore aching muscles.
- Cover with a warm, dry cloth if desired
- Keep clothing loose about throat/chest to help vapors reach the nose/mouth
- repeat up to 3 times per 24 hours or as directed by doctor
- children under 2 years: do not use

Other information

- store at room temperature.

Inactive ingredients

myristica fragrans (nutmeg) kernel oil, petrolatum, thuja occidentalis bark extract, thymol, turpentine

Package label

Vida Mia Chest Rub